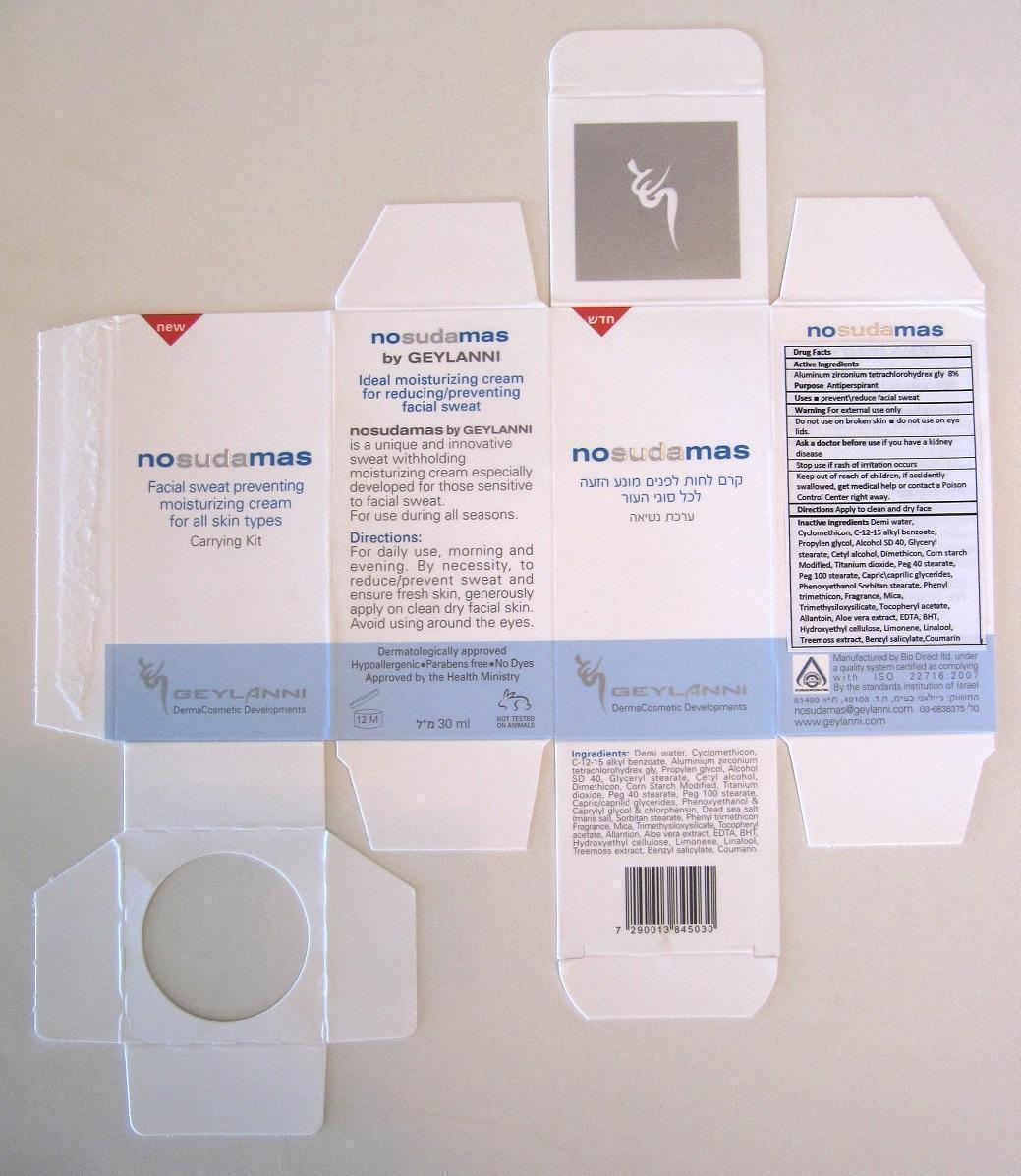 DRUG LABEL: nosudamas Carrying Kit
NDC: 70064-001 | Form: CREAM
Manufacturer: Geylanni International cosmetic developments LTD
Category: otc | Type: HUMAN OTC DRUG LABEL
Date: 20150904

ACTIVE INGREDIENTS: Aluminum Zirconium Tetrachlorohydrex GLY 80 mg/1 mL
INACTIVE INGREDIENTS: CYCLOMETHICONE; ALKYL (C12-15) BENZOATE; PROPYLENE GLYCOL; ALCOHOL; GLYCERYL MONOSTEARATE; DIMETHICONE; STARCH, CORN; TITANIUM DIOXIDE; PEG-40 STEARATE; PEG-100 STEARATE; PEG-6 CAPRYLIC/CAPRIC GLYCERIDES; PHENOXYETHANOL; SORBITAN MONOSTEARATE; PHENYL TRIMETHICONE; MICA; TRIMETHYLSILOXYSILICATE (M/Q 0.6-0.8); ALPHA-TOCOPHEROL ACETATE; ALLANTOIN; ALOE VERA LEAF; EDETIC ACID; BUTYLATED HYDROXYTOLUENE; HYDROXYETHYL CELLULOSE (100 MPA.S AT 2%); LIMONENE, (+)-; LINALOOL, (+/-)-; PSEUDEVERNIA FURFURACEA; BENZYL SALICYLATE; COUMARIN

nosudamas

Actives

Aluminum Zirconium Tetrachlorohydrex GLY 8%

Inactives

CYCLOMETHICONE
ALKYL (C12-15) BENZOATE
PROPYLENE GLYCOL
ALCOHOL
GLYCERYL MONOSTEARATE
DIMETHICONE
STARCH, CORN
TITANIUM DIOXIDE
PEG-40 STEARATE
PEG-100 STEARATE
PEG-6 CAPRYLIC/CAPRIC GLYCERIDES
PHENOXYETHANOL
SORBITAN MONOSTEARATE
PHENYL TRIMETHICONE
MICA
TRIMETHYLSILOXYSILICATE (M/Q 0.6-0.8)
ALPHA-TOCOPHEROL ACETATE
ALLANTOIN
ALOE VERA LEAF
EDETIC ACID
BUTYLATED HYDROXYTOLUENE
HYDROXYETHYL CELLULOSE (100 MPA.S AT 2%)
LIMONENE, (+)-
LINALOOL, (+/-)-
PSEUDEVERNIA FURFURACEA
BENZYL SALICYLATE
COUMARIN

Purpose

Antiprespirant

Usage

Prevent/reduce facial sweat

Ask Doctor Before Use

Ask a doctor before use if you have any kidney deseases

Stop Using

Stop using if irration occurs

Directions for Use

Apply to clean and dry face

Keep out of reach of children, if accidently swallowed get medical help or contact a Poision Control Center right away.

Warning

For external use only